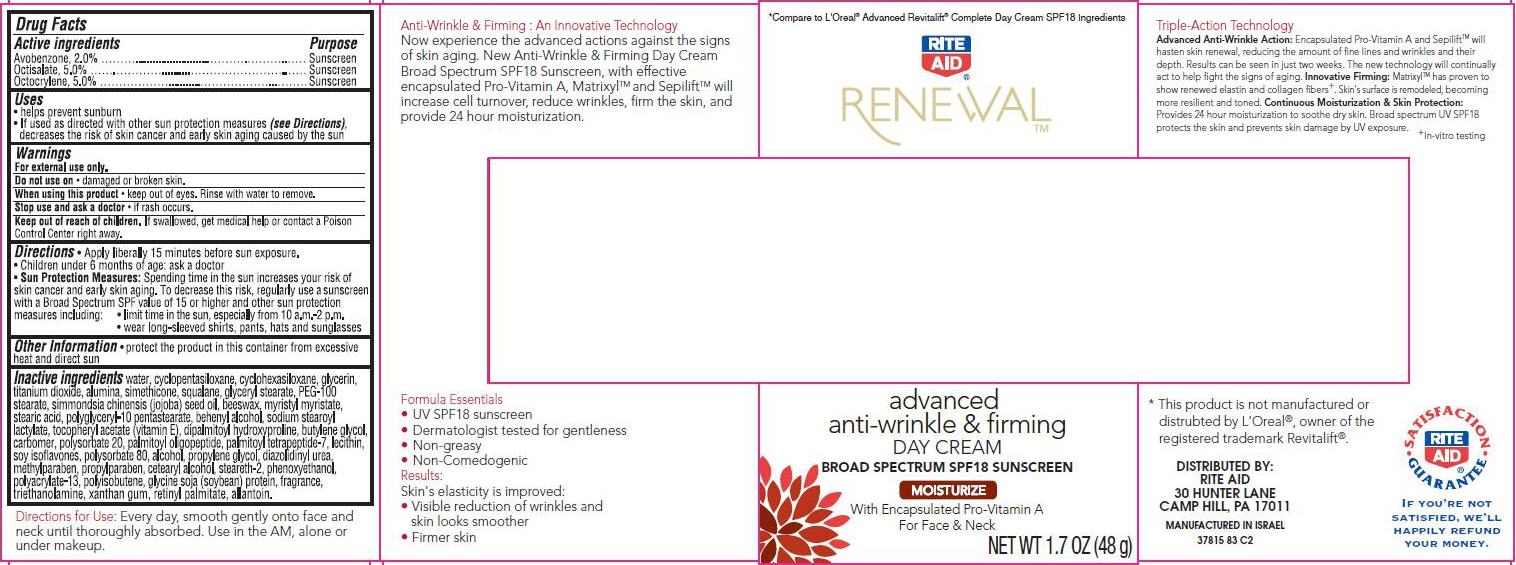 DRUG LABEL: Advanced Firming and Anti Wrinkle
NDC: 11822-9785 | Form: CREAM
Manufacturer: Rite Aid Corporation
Category: otc | Type: HUMAN OTC DRUG LABEL
Date: 20140110

ACTIVE INGREDIENTS: AVOBENZONE 2 g/100 g; OCTISALATE 5 g/100 g; OCTOCRYLENE 5 g/100 g
INACTIVE INGREDIENTS: WATER; CYCLOMETHICONE 5; CYCLOMETHICONE 6; GLYCERIN; TITANIUM DIOXIDE; ALUMINUM OXIDE; DIMETHICONE; SQUALANE; GLYCERYL MONOSTEARATE; PEG-100 STEARATE; JOJOBA OIL; YELLOW WAX; MYRISTYL MYRISTATE; STEARIC ACID; DOCOSANOL; SODIUM STEAROYL LACTYLATE; .ALPHA.-TOCOPHEROL ACETATE; DIPALMITOYL HYDROXYPROLINE; BUTYLENE GLYCOL; POLYSORBATE 20; PALMITOYL OLIGOPEPTIDE; PALMITOYL TETRAPEPTIDE-7; LECITHIN, SOYBEAN; SOY ISOFLAVONES; POLYSORBATE 80; ALCOHOL; PROPYLENE GLYCOL; DIAZOLIDINYL UREA; METHYLPARABEN; PROPYLPARABEN; CETOSTEARYL ALCOHOL; STEARETH-2; PHENOXYETHANOL; SOYBEAN; TROLAMINE; XANTHAN GUM; VITAMIN A PALMITATE; ALLANTOIN; CARBOMER COPOLYMER TYPE B (ALLYL PENTAERYTHRITOL CROSSLINKED); POLYISOBUTYLENE (1000 MW)

Renewal™ Advanced Anti-Wrinkle & Firming Day Cream

Active ingredient

Avobenzone 2.0%

Octisalate 5.0%

Octocrylene 5.0%

Purpose

Sunscreen

Uses

- helps prevent sunburn
- If used as directed with other sun protection measures (see Directions), decreases the risk of skin cancer and early skin aging caused by the sun

Warnings

For external use only.

Do not use on

- damaged or broken skin.

When using this product

- keep out of eyes. Rinse with water to remove.

Stop use and ask a doctor

- if rash occurs.

Keep Out of Reach of Children.

If swallowed, get medical help or contact a Poison Control Center right away.

Directions

- Apply liberally 15 minutes before sun exposure.
- Children under 6 months of age: ask a doctor
- Sun Protection Measures: Spending time in the sun increases your risk of skin cancer and early skin aging. To decrease this risk, regularly use a sunscreen with a Broad Spectrum SPF value of 15 or higher and other sun protection measures including:
  - limit time in the sun, especially from 10 a.m. - 2 p.m.
  - wear long-sleeved shirts, pants, hats and sunglasses

Other Information

- protect the product in this container from excessive heat and direct sun

Inactive ingredients

water, cyclopentasiloxane, cyclohexasiloxane, glycerin, titanium dioxide, alumina, simethicone, squalane, glyceryl stearate, PEG-100 stearate, simmondsia chinensia (jojoba) seed oil, beeswax, myristyl myristate, stearic acid, polyglyceryl-10 pentastearate, bhenyl alcohol, sodium steroyl lactylate, tocopheryl acetate (vitamin E), dipalmitoyl hydroxyproline, butylene glycol, carbomer, polysorbate 20, palmitoyl oiligopeptide, palmitoyl tetrapeptide-7, lecithin, soy isoflavones, polysorbate 80, alcohol, propylene glycol, diazolidinyl urea, methylparaben, propylparaben, cetearyl alcohol, steareth-2, phenoxyethanol, polyacrylate-13, polyisobutene, glycine soja (soybean) protein, fragrance, triethanolamine, xanthan gum, retinyl palmitate, allantoin

Package/Label Principal Display Panel

Rite Aid RENEWAL™
advanced anti-wrinkle & firming DAY CREAM Broad Spectrum SPF18 Sunscreen

MOISTURIZE

With Encapsulated Pro-Vitamin A
For Face & Neck

NET WT 1.7 OZ (48 g)

*Compare to L'Oreal® Advanced Revitalift® Complete Day Cream SPF18 Ingredients

DISTRIBUTED BY:
RITE AID
30 HUNTER LANE
CAMP HILL, PA 17011

Manufactured in Israel
37815 83 C2

Carton Label